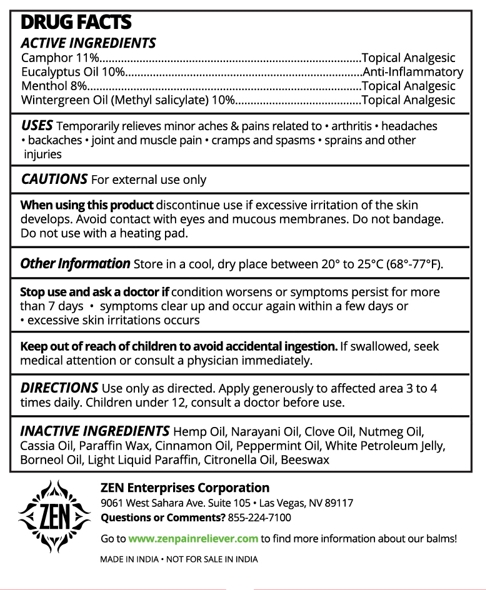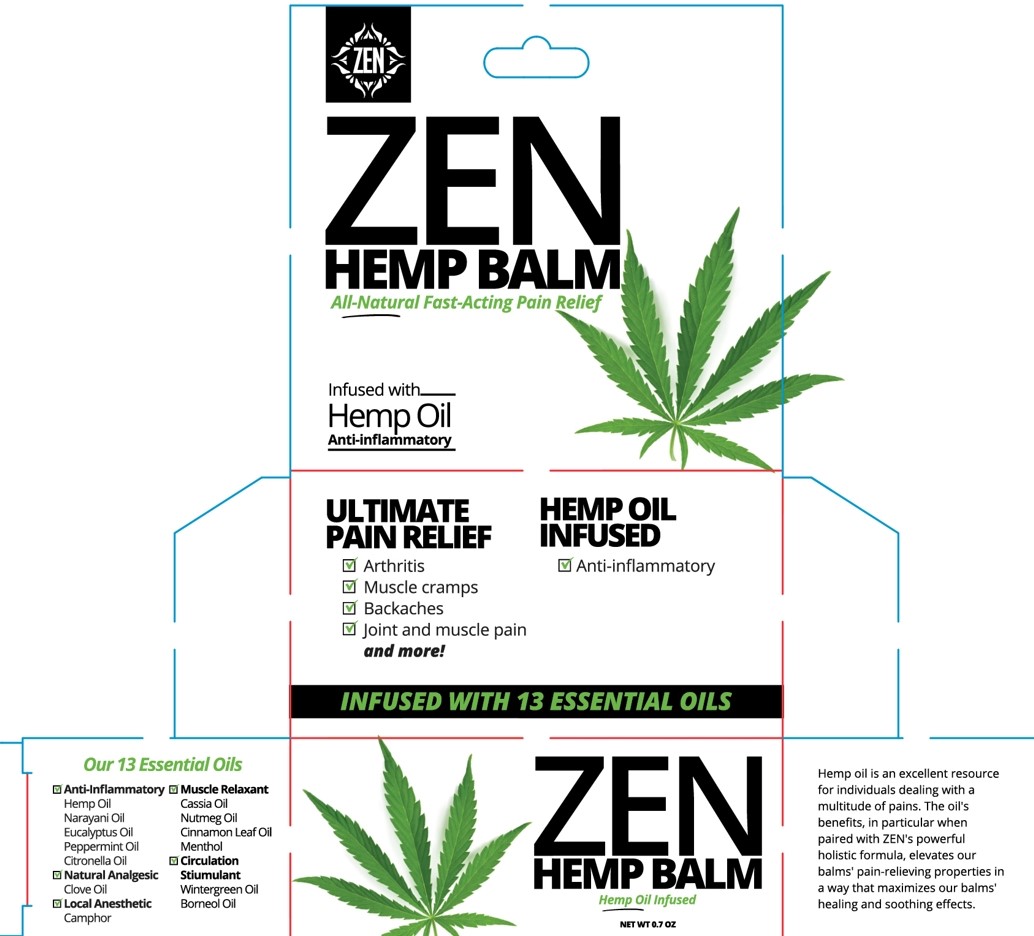 DRUG LABEL: ZEN HEMP Balm
NDC: 73048-005 | Form: OINTMENT
Manufacturer: Zen Enterprises LLC
Category: otc | Type: HUMAN OTC DRUG LABEL
Date: 20240828

ACTIVE INGREDIENTS: EUCALYPTUS OIL 10 g/100 g; CAMPHOR (NATURAL) 11 g/100 g; MENTHOL 8 g/100 g; METHYL SALICYLATE 10 g/100 g
INACTIVE INGREDIENTS: CANNABIS SATIVA SEED OIL; YELLOW WAX; PETROLATUM; LIGHT MINERAL OIL; CINNAMON OIL; NUTMEG OIL; PARAFFIN; BORNEOL; CITRONELLA OIL; PEPPERMINT OIL; CLOVE OIL; CHINESE CINNAMON OIL

ZEN HEMP Balm

Active ingredients

Camphor 11%

Eucalyptus Oil 10%

Menthol 8%

Wintergreen Oil (Methyl salicylate) 10%

Purpose

Topical Analgesic

Anti-Inflammatory

Topical Analgesic

Topical Analgesic

Uses

Temporarily relieves minor aches & pains releated to arthritis, headaches, backaches, joints and muscle pain, cramps and spasms, sprains and other injuries

Cautions

For external use only

When using this product discontinue use if excessive irritation of the skin develops. Avoid contact with eyes and mucous membranes. Do not bandage. Do not use with a heating pad.

Stop use and ask a doctor if condition worsens or symptoms persist for more than 7 days.

- symptoms cear up and occur again within a few days or
- excessive skin irritation occurs.

Keep out of reach of children to avoid accidental ingestion.

If swallowed, seek medical attention or consult a physician immediately.

Other Information

Store in a cool, dry place between 20º to 25 ºC (68º-77ºF)

Directions

Use only as directed. Apply generously to affected area 3 to 4 times daily. Children under 12, consult a doctor before use.

Inactive ingredients

Hemp Oil

Clove Oil

Nutmeg Oil

Cassia Oil

Paraffin Wax

Cinnamon Oil

Pwppermint Oil

White Petroleum Jelly

Borneol Oil Light Liquid Paraffin

Citronella Oil

Beeswax